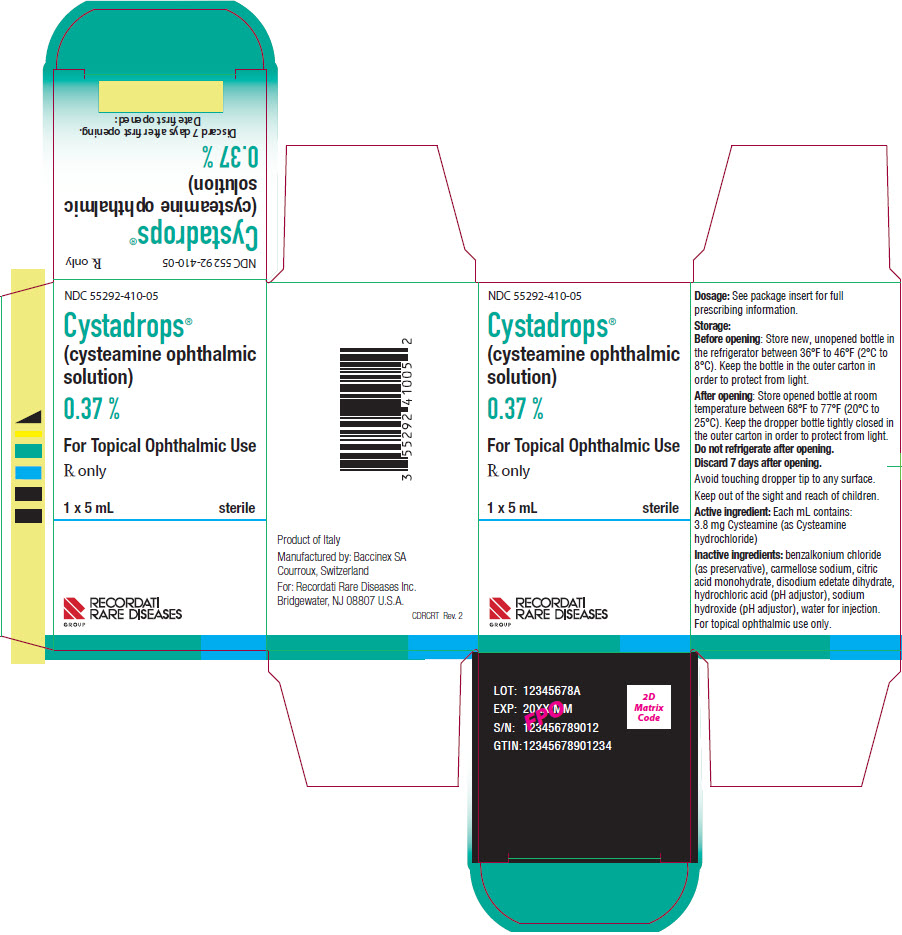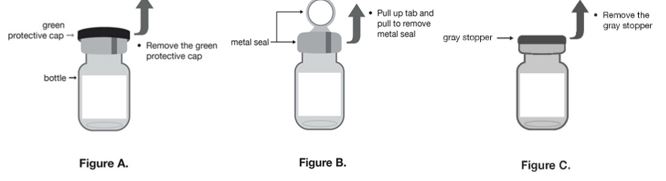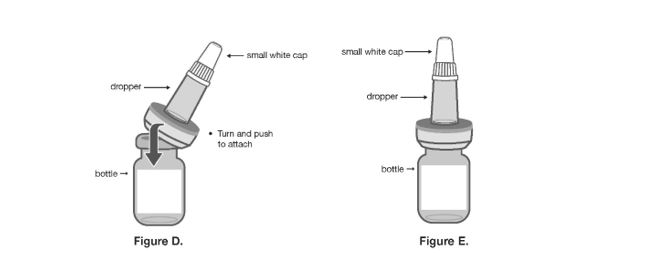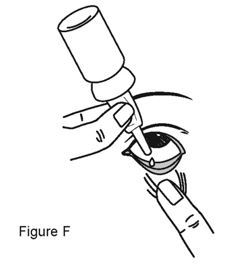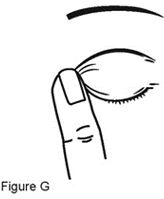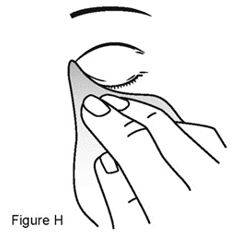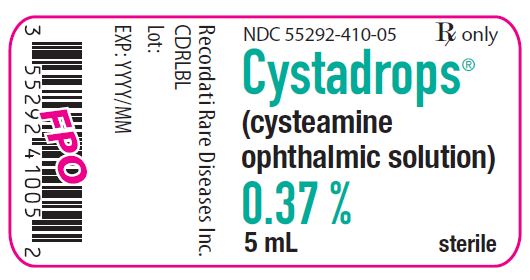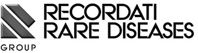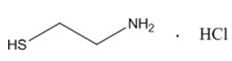 DRUG LABEL: CYSTADROPS
NDC: 55292-410 | Form: SOLUTION
Manufacturer: RECORDATI RARE DISEASES, INC.
Category: prescription | Type: HUMAN PRESCRIPTION DRUG LABEL
Date: 20250606

ACTIVE INGREDIENTS: Cysteamine Hydrochloride 3.5 mg/1 mL
INACTIVE INGREDIENTS: Benzalkonium Chloride; Carboxymethylcellulose Sodium, Unspecified; Citric Acid Monohydrate; Edetate Disodium; Hydrochloric Acid; Sodium Hydroxide; Water

HIGHLIGHTS OF PRESCRIBING INFORMATION

These highlights do not include all the information needed to use CYSTADROPS safely and effectively. See full prescribing information for CYSTADROPS .
CYSTADROPS® (cysteamine ophthalmic solution) 0.37%, for topical ophthalmic use
Initial U.S. Approval: 1994

1 INDICATIONS AND USAGE

CYSTADROPS is a cystine-depleting agent indicated for the treatment of corneal cystine crystal deposits in adults and children with cystinosis. (1)

2 DOSAGE AND ADMINISTRATION

Instill one drop of CYSTADROPS in each eye, 4 times a day during waking hours. (2.1)

3 DOSAGE FORMS AND STRENGTHS

Ophthalmic solution containing 3.8 mg/mL of cysteamine (0.37%). (3)

4 CONTRAINDICATIONS

None. (4)

5 WARNINGS AND PRECAUTIONS

To minimize the risk of contamination, do not touch the dropper tip to any surface. Keep bottle tightly closed when not in use. (5.1)

6 ADVERSE REACTIONS

The most common adverse reactions (≥ 10%) are eye pain, vision blurred, eye irritation, ocular hyperaemia, instillation site discomfort, eye pruritus, lacrimation increased, and ocular deposits. (6)

To report SUSPECTED ADVERSE REACTIONS, contact Recordati Rare Diseases Inc. at 1-888-575-8344, or FDA at 1-800-FDA-1088 or www.fda.gov/medwatch.

FULL PRESCRIBING INFORMATION

1 INDICATIONS AND USAGE

CYSTADROPS is a cystine-depleting agent indicated for the treatment of corneal cystine crystal deposits in adults and children with cystinosis.

2 DOSAGE AND ADMINISTRATION

2.1 Dosage Information

Instill one drop of CYSTADROPS in each eye, 4 times a day during waking hours.

Do not touch dropper tip to the eyelids, surrounding areas, or any surface, as this may contaminate the solution.

In case of concomitant therapy with other topical ocular products, an interval of 10 minutes should be allowed between successive applications. Eye ointments should be administered last.

If the patient misses an instillation, the patient should be told to administer a dose as soon as feasible and then continue the treatment with the next scheduled instillation. Discard bottle 7 days after first opening.

2.2 Preparation for Administration

1. Patients should be advised to store new unopened CYSTADROPS bottles in the refrigerator in the original carton between 36°F to 46°F (2°C to 8°C).
2. Each week, one new bottle should be removed from the refrigerator. Patients are to write the date the bottle was opened in the space on the carton. After first opening, store opened CYSTADROPS at room temperature between 68°F to 77°F (20°C to 25°C). Do not refrigerate after opening.
3. Patients are to wash their hands carefully in order to avoid microbiological contamination of the content in the bottle.
4. Remove the green protective cap (see Figure A).
5. Remove the metal seal (see Figure B).
6. Remove the gray stopper (see Figure C) from the bottle.
7. Do not touch the opening of the bottle after removing the gray stopper.

1. Take the dropper out of its packaging, without touching the end intended to be attached to the bottle, attach it (see Figure D) to the bottle and do not remove it.
2. Patients should be advised not to lose the small white cap that comes on the top of the dropper (see Figure E). Keep the small white cap tightly closed when not in use.
3. Instill one drop of CYSTADROPS in each eye, 4 times a day during waking hours.
4. At the end of 7 days, patients should discard the bottle. There may be medication left in the bottle; however, the bottle must be discarded by the patient because the medication is only stable for 7 days after first opening.

3 DOSAGE FORMS AND STRENGTHS

Ophthalmic solution containing 3.8 mg/mL of cysteamine (0.37%).

4 CONTRAINDICATIONS

None.

5 WARNINGS AND PRECAUTIONS

5.1 Contamination of Tip and Solution

To minimize contaminating the dropper tip and solution, care should be taken not to touch the eyelids or surrounding areas with the dropper tip of the bottle. Keep bottle tightly closed when not in use.

5.2 Benign Intracranial Hypertension

There have been reports of benign intracranial hypertension (or pseudotumor cerebri) associated with oral cysteamine treatment that has resolved with the addition of diuretic therapy. There have also been reports associated with ophthalmic use of cysteamine; however, all of these patients were on concurrent oral cysteamine.

5.3 Contact Lens Use

CYSTADROPS contains benzalkonium chloride, which may be absorbed by soft contact lenses. Contact with soft contact lenses should be avoided. Contact lenses should be removed prior to application of solution and may be reinserted 15 minutes following its administration [see Patient Counseling Information (17)].

6 ADVERSE REACTIONS

6.1 Clinical Trials Experience

Because clinical trials are conducted under widely varying conditions, adverse reaction rates observed in clinical trials of a drug cannot be directly compared to rates in the clinical trials of another drug and may not reflect the rates observed in practice.

The most common adverse reactions (≥ 10%) reported during clinical trials were eye pain, vision blurred, eye irritation, ocular hyperaemia, instillation site discomfort, eye pruritus, lacrimation increased, and ocular deposits.

8 USE IN SPECIFIC POPULATIONS

8.1 Pregnancy

Risk Summary
There are no adequate and well-controlled studies of ophthalmic cysteamine in pregnant women to inform any drug associated risks. Oral administration of cysteamine to pregnant rats throughout the period of organogenesis was teratogenic at doses 240 to 960 times the recommended human ophthalmic dose (based on body surface area) [see Data]. CYSTADROPS should be used during pregnancy only if the potential benefit justifies the potential risk to the fetus.

The estimated background risk of major birth defects and miscarriage for the indicated population is unknown. All pregnancies have a background risk of birth defect, loss, or other adverse outcomes In the U.S. general population, the estimated background risk of major birth defects and miscarriage in clinically recognized pregnancies is 2% to 4% and 15% to 20%, respectively.

Data
Animal data
Teratology studies have been performed in rats at oral doses in the range of 37.5 mg/kg/day to 150 mg/kg/day (240 to 960 times the recommended human ophthalmic dose based on body surface area) and have shown cysteamine bitartrate to be teratogenic. Observed teratogenic findings were intrauterine death, cleft palate, kyphosis, heart ventricular septal defects, microcephaly, exencephaly, and growth deficits.

8.2 Lactation

Risk Summary

There is no information regarding the presence of cysteamine in human milk, the effects on the breastfed infants, or the effects on milk production. Cysteamine administered orally is present in milk of lactating rats. It is not known whether measurable levels of cysteamine would be present in maternal milk following topical ocular administration of CYSTADROPS. The developmental and health benefits of breastfeeding should be considered along with the mother's clinical need for CYSTADROPS and any potential adverse effects on the breastfed child from CYSTADROPS or from the underlying maternal conditions.

8.4 Pediatric Use

The safety and effectiveness of CYSTADROPS has been established in pediatric patients. Use of CYSTADROPS is supported by adequate and well controlled trials in pediatric patients and additional experience supporting the safety of CYSTADROPS.

8.5 Geriatric Use

Clinical studies of CYSTADROPS did not include sufficient numbers of subjects aged 65 and over to determine whether they respond differently from younger subjects. Other reported clinical experience has not identified differences in responses between the elderly and younger patients.

8.6 Renal Impairment

The effect of renal impairment on the pharmacokinetics of cysteamine following ophthalmic administration of cysteamine ophthalmic solution has not been evaluated. Clearance of cysteamine from the conjunctival sac of the eye is not dependent on renal function and the total systemic dose is negligible, so impaired renal function is unlikely to affect total body clearance.

The total daily ophthalmic dose is less than 4% of the recommended oral daily dose of cysteamine; thus, the systemic exposure following ophthalmic administration is expected to be negligible compared to oral administration.

11 DESCRIPTION

CYSTADROPS is a sterile, viscous, ophthalmic solution containing 3.8 mg/mL of cysteamine (0.37%) equivalent to 5.6 mg/mL of cysteamine hydrochloride (0.55%). Cysteamine is a cystine- depleting agent which lowers the cystine content of cells in patients with cystinosis.

Molecular Formula: C2H7NS HCl

Molecular Weight: 113.61

Each milliliter of CYSTADROPS contains: Active: cysteamine 3.8 mg (equivalent to cysteamine hydrochloride 5.6 mg); Preservative: benzalkonium chloride 0.1 mg; Inactive Ingredients: carmellose sodium, citric acid monohydrate, disodium edetate dihydrate, hydrochloric acid and sodium hydroxide (to adjust pH to 4.6-5.4), and water for injection.

12 CLINICAL PHARMACOLOGY

12.1 Mechanism of Action

Cysteamine acts as a cystine-depleting agent by converting cystine to cysteine and cysteine-cysteamine mixed disulfides and reduces corneal cystine crystal accumulation.

12.3 Pharmacokinetics

The peak plasma concentration of cysteamine following ocular administration of cysteamine ophthalmic solution in humans is unknown, because all patients concomitantly received oral cysteamine and the total daily ophthalmic dose is less than 4% of the recommended oral daily dose of cysteamine.

13 NONCLINICAL TOXICOLOGY

13.1 Carcinogenesis, Mutagenesis, Impairment of Fertility

Carcinogenesis
Cysteamine has not been tested for its carcinogenic potential in long-term animal studies.

Mutagenesis
Cysteamine was not mutagenic in the Ames test. It produced a negative response in an in vitro sister chromatid exchange assay in human lymphocytes but a positive response in a similar assay in hamster ovarian cells.

Impairment of Fertility
Repeat breeding reproduction studies were conducted in male and female rats. Cysteamine was found to have no effect on fertility and reproductive performance at an oral dose of 75 mg/kg/day (480 times the recommended human ophthalmic dose based on body surface area). At an oral dose of 375 mg/kg/day (2,400 times the recommended human ophthalmic dose based on body surface area), it reduced the fertility of the adult rats and the survival of their offspring.

14 CLINICAL STUDIES

Clinical safety and efficacy of CYSTADROPS were assessed in two studies: a single-arm study conducted for 5 years (OCT-1) and a randomized controlled study conducted for 90 days (CHOC).

In the OCT-1 study, 8 patients with cystinosis (2 males and 6 females) with a mean age of 12.1 ± 4.6 (range: 7.0 – 21.0) were enrolled and received a median of 4 drops/eye/day of CYSTADROPS. In CHOC study, 32 patients with cystinosis (15 males and 17 females) with a mean age of 17.1 ± 13.0 (range: 2.9 – 62.6) were enrolled and received a median of 4 drops/eye/day. Fifteen patients were exposed to CYSTADROPS and 16 were exposed to cysteamine hydrochloride 0.1% (control arm).

Efficacy was assessed with In-Vivo Confocal Microscopy total score (IVCM score) by quantifying the cystine crystals in the cornea. A decrease in IVCM total score from baseline indicated a reduction in corneal crystals.

In the CHOC study, after 30 and 90 days of treatment with CYSTADROPS, 12% and 40% reduction in the total IVCM total score across all corneal layers was observed from baseline, respectively. CYSTADROPS demonstrated greater reduction compared to the control arm at 90 days. The average reduction in IVCM total score was 4.6 in the CYSTADROPS arm and 0.5 in the control arm, mean difference 3.8 (95% CI: (2.1, 5.6)).

In the OCT-1 study, a mean decrease in corneal cystine crystal deposits of 30%, in comparison with baseline, was maintained over the 60 month period of the study.

16 HOW SUPPLIED/STORAGE AND HANDLING

CYSTADROPS (cysteamine ophthalmic solution) 0.37% is supplied as a 5 mL sterile viscous solution in a 10 mL amber glass bottle closed by a bromobutyl stopper and sealed with an aluminum tear-off cap. A PVC dropper applicator with HDPE closure is packed separately and included in each carton box.

Each carton box (NDC 55292-410-05) contains 1 bottle (NDC 55292-410-05) and 1 dropper applicator individually wrapped.

Before First Opening: Before opening, store new, unopened CYSTADROPS in the refrigerator between 36°F to 46°F (2°C to 8°C). Keep the bottle in the outer carton in order to protect from light.

After First Opening: After opening, store opened CYSTADROPS at room temperature between 68°F to 77°F (20°C to 25°C). Do not refrigerate after opening. Keep the dropper bottle tightly closed in the outer carton in order to protect from light. Discard 7 days after first opening.

17 PATIENT COUNSELING INFORMATION

Advise the patient to read the FDA-approved patient labeling (Instructions for Use).

Preparation for Administration and Storage of Bottles

1. Advise patients to store new unopened bottles in the refrigerator in the original carton.
2. Each week, one new bottle should be removed from the refrigerator. Advise patients to write the date the bottle was opened in the space on the carton. After first opening, keep the bottle tightly closed and store at room temperature in the original carton.
3. Patients are to wash their hands carefully in order to avoid microbiological contamination of the content in the bottle.
4. Remove the green protective cap (see Figure A).
5. Remove the metal seal (see Figure B).
6. Remove the gray stopper (see Figure C) from the bottle.
7. Do not touch the opening of the bottle after removing the gray stopper.

1. Take the dropper out of its packaging, without touching the end intended to be attached to the bottle, attach it (see Figure D) to the bottle and do not remove it.
2. Patients should be advised not to lose the small white cap (see Figure E) that comes on the top of the dropper. Keep the small white cap tightly closed when not in use.
3. Instill one drop of CYSTADROPS in each eye, 4 times a day during waking hours.
4. Instruct patients to discard the bottle at the end of 7 days. There may be medication left in the bottle; however, the bottle must be discarded by the patient because the medication is only stable for 7 days after first opening.

Risk of Contamination

Advise patients not to touch the eyelid or surrounding areas with the dropper tip of the bottle. The cap should remain on the bottle when not in use.

Contact Lens Use

Advise patients that contact lenses should be removed prior to application of CYSTADROPS. Contact lenses may be reinserted 15 minutes following CYSTADROPS administration [see Warnings and Precautions (5.3)].

Topical Ophthalmic Use

Advise patients that CYSTADROPS is for topical ophthalmic use.

Missed Dose

If the patient misses an instillation, instruct the patient to administer a dose as soon as feasible and then to continue the treatment with the next scheduled instillation.

Manufactured by: Baccinex SA, 2822 Courroux, Switzerland

Manufactured for: Recordati Rare Diseases Inc., Bridgewater, NJ 08807, U.S.A.

This product label may have been updated. For the most recent prescribing information, please visit www.recordatirarediseases.com/us.

PATIENT INFORMATION

INSTRUCTIONS FOR USE
CYSTADROPS® (sys-tah-drops)
(cysteamine ophthalmic solution)
for topical ophthalmic use
Read this Instructions for Use carefully before you start using CYSTADROPS and each time you get a refill; there may be new information. This leaflet does not take the place of talking to your healthcare provider about your medical condition or treatment.
Important information:
• | Use CYSTADROPS exactly as your healthcare provider tells you to use it.
• | CYSTADROPS is for use in the eyes.
• | Wash your hands before each use.
• | If you use CYSTADROPS with other eye medicines, you should wait at least 10 minutes between using CYSTADROPS and your other eye medicines.
• | If you wear contact lenses, remove them before using CYSTADROPS. You should wait at least 15 minutes after using CYSTADROPS, before placing your contact lenses back in your eyes.
• | Do not let the CYSTADROPS dropper touch your eyelids or any other surfaces.
Storing CYSTADROPS:
• | Before opening, store new, unopened CYSTADROPS in the refrigerator between 36°F to 46°F (2°C to 8°C).
• | After first opening, store opened CYSTADROPS at room temperature between 68°F to 77°F (20°C to 25°C). Do not refrigerate after opening.
• | Keep CYSTADROPS in the original carton to protect from light.
• | Keep the CYSTADROPS dropper bottle tightly closed when not in use.
• | Throw away any unused CYSTADROPS 7 days after opening.
• | Keep CYSTADROPS and all medicines out of the reach of children.
Supplies needed:
• | CYSTADROPS bottle and dropper
• | mirror
• | tissue
Using CYSTADROPS:
• | Use 1 drop in each eye, four times a day.
• | If you miss a dose, administer the missed dose as soon as possible and then use the drops at your next regular scheduled time.
Step 1: Before using a CYSTADROPS bottle for the first time
• | Check the expiration date on the CYSTADROPS bottle before use. Do not use CYSTADROPS if the expiration date has passed.
• | After opening a CYSTADROPS bottle, allow it to reach room temperature before using it for the first time.
• | After opening a CYSTADROPS bottle for the first time, write the date of opening in the space provided on the carton.
• | Wash your hands carefully in order to avoid contamination of the contents in the bottle.
• | Remove the green protective cap (Figure A).
• | Remove the metal seal (Figure B).
• | Remove the gray stopper (Figure C).
• | Do not touch the opening of the bottle after removing the gray stopper.
• | Place the opened bottle on a flat surface.
• | Take the dropper out of its packaging. Do not touch the end of the dropper that will be attached to the bottle. Attach the dropper (Figure D) to the bottle. After attaching the dropper to the bottle, do not remove the dropper from the bottle (Figure E).
• | Make sure that you do not lose the small white cap (Figure E) that comes on the top of the dropper.
Step 2: Before using CYSTADROPS
• | Check the opening date that you wrote down on the carton. Do not use CYSTADROPS if more than 7 days have passed since the opening date.
• | Get the CYSTADROPS dropper bottle, mirror, and tissue.
• | Wash your hands.
Step 3: Using the CYSTADROPS dropper bottle
• | Twist the small white cap to remove it from the dropper. Do not throw the small white cap away.
• | Hold the CYSTADROPS dropper bottle with the dropper pointing down, between your thumb and fingers. If no medicine fills the dropper, move the CYSTADROPS dropper bottle up and down until medicine fills the dropper.
• | Tilt your head back. Pull down your lower eyelid with a clean finger and look up (Figure F). The medicine will go into the space between your lower eyelid and your eye.
• | Use the mirror to help you bring the dropper bottle tip close to the eye.
• | Do not let the CYSTADROPS dropper touch your eyelids or any other surfaces.
• | Gently squeeze the dropper to release 1 drop of CYSTADROPS.
• | If a drop misses your eye, try again.
• | After using CYSTADROPS, close your eye and press a finger into the corner of your eye by the nose (Figure G), then gently massage your upper eyelid to spread the CYSTADROPS over the eye.
• | Remove any medicine around the eye with a tissue (Figure H).
• | Repeat Step 3 for the other eye.
• | Replace the small white cap on the dropper immediately after use.
This Instructions for Use has been approved by the U.S. Food and Drug Administration.
Manufactured by: Baccinex SA, 2822 Courroux, Switzerland
Manufactured for: Recordati Rare Diseases Inc., Bridgewater, NJ 08807, U.S.A.
Approved: 08/2020

PRINCIPAL DISPLAY PANEL - 5 mL Bottle Box

NDC 55292-410-05

Cystadrops®
(cysteamine ophthalmic
solution)

0.37 %

For Topical Ophthalmic Use

Rx only

1 x 5 mL
sterile

RECORDATI
RARE DISEASES
GROUP

PACKAGE LABEL.PRINCIPAL DISPLAY PANEL

NDC 55292-410-05
Rx only
Cystadrops®
(cysteamine ophthalmic solution)
0.37 %
5 mL
sterile
Recordati Rare Diseases Inc.
CDRLBL
Lot:
EXP: YYYY/MM